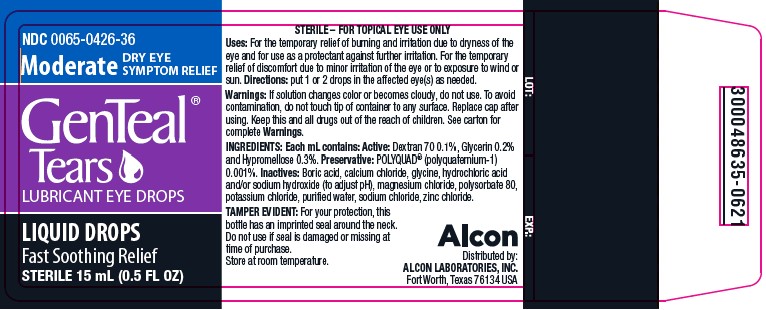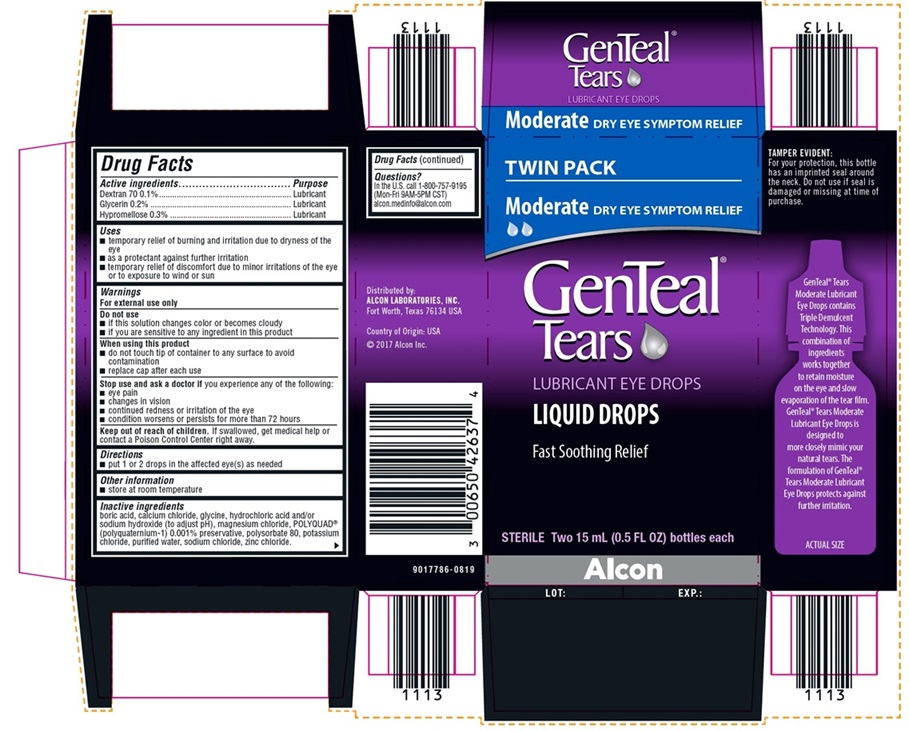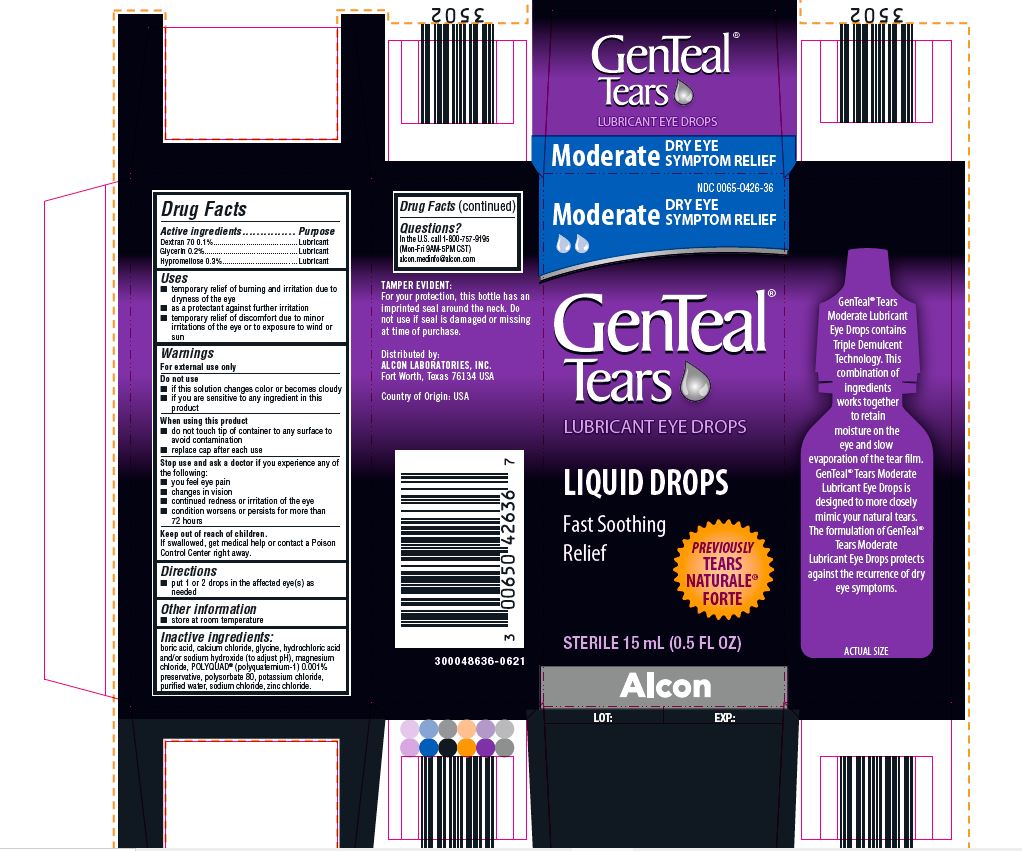 DRUG LABEL: GenTeal Tears (Moderate)
NDC: 0065-0426 | Form: SOLUTION/ DROPS
Manufacturer: Alcon Laboratories, Inc.
Category: otc | Type: HUMAN OTC DRUG LABEL
Date: 20231215

ACTIVE INGREDIENTS: Dextran 70 1 mg/1 mL; Glycerin 2 mg/1 mL; Hypromelloses 3 mg/1 mL
INACTIVE INGREDIENTS: Boric Acid; Calcium Chloride; Glycine; Hydrochloric Acid; Sodium Hydroxide; Magnesium Chloride; Polidronium Chloride; Polysorbate 80; Potassium Chloride; Water; Sodium Chloride; Zinc Chloride

Drug Facts

ACTIVE INGREDIENT

Active ingredients | Purpose
Dextran 70 0.1% | Lubricant
Glycerin 0.2% | Lubricant
Hypromellose 0.3% | Lubricant

Uses

- temporary relief of burning and irritation due to dryness of the eye
- as a protectant against further irritation
- temporary relief of discomfort due to minor irritations of the eye or to exposure to wind or sun

Warnings

For external use only

Do not use

- if this solution changes color or becomes cloudy
- if you are sensitive to any ingredient in this product

When using this product

- do not touch tip of container to any surface to avoid contamination
- replace cap after each use

Stop use and ask a doctor if you experience any of the following:

- you feel eye pain
- changes in vision
- continued redness or irritation of the eye
- condition worsens or persists for more than 72 hours

Keep out of reach of children.

If swallowed, get medical help or contact a Poison Control Center right away.

Directions

- put 1 or 2 drops in the affected eye(s) as needed

Other Information

- store at room temperature

Inactive ingredients:

boric acid, calcium chloride, glycine, hydrochloric acid and/or sodium hydroxide (to adjust pH), magnesium chloride, POLYQUAD* (polyquaternium-1) 0.001% preservative, polysorbate 80, potassium chloride, purified water, sodium chloride, zinc chloride.

Questions?

In the U.S. call 1-800-757-9195
(Mon-Fri 9AM-5PM CST)
alcon.medinfo@alcon.com

PRINCIPAL DISPLAY PANEL

NDC 0065-0426-36
Moderate DRY EYE SYMPTOM RELIEF
GenTeal® Tears
LUBRICANT EYE DROPS
LIQUID DROPS
Fast Soothing Relief
PREVIOUSLY TEARS NATURALE® FORTE
STERILE 15 mL (0.5 FL OZ)
Alcon
TAMPER EVIDENT:
For your protection, this bottle has an
imprinted seal around the neck. Do
not use if seal is damaged or missing
at time of purchase.
Distributed by:
ALCON LABORATORIES, INC.
Fort Worth, Texas 76134 USA
Country of Origin: USA
300048636-0621

NDC 0065-0426-37
TWIN PACK
Moderate DRY EYE SYMPTOM RELIEF
GenTeal® Tears
LUBRICANT EYE DROPS
LIQUID DROPS
Fast Soothing Relief
STERILE Two 15 mL (0.5 FL OZ) bottles each
Alcon
TAMPER EVIDENT:
For your protection, this bottle has an
imprinted seal around the neck. Do
not use if seal is damaged or missing
at time of purchase.
Distributed by:
ALCON LABORATORIES, INC.
Fort Worth, Texas 76134 USA
Country of Origin: USA
©2017 Alcon Inc.
9017786-0819

NDC 0065-0426-36
Moderate DRY EYE SYMPTOM RELIEF
GenTeal® Tears
LUBRICANT EYE DROPS
LIQUID DROPS
Fast Soothing Relief
STERILE 15 ml (0.5 FL OZ)
STERILE-FOR TOPICAL EYE USE ONLY
Uses: For the temporary relief of burning and irritation due to dryness of the eye and for use as a protectant against further irritation. For the temporary relief of discomfort due to minor irritation of the eye or to exposure to wind or sun. Directions: put 1 or 2 drops in the affected eye(s) as needed.
Warnings: If solution changes color or becomes cloudy, do not use. To avoid contamination, do not touch tip of container to any surface. Replace cap after using. Keep this and all drugs out of the reach of children. See carton for complete Warnings.
INGREDIENTS: Each mL contains: Active: Dextran 70 0.1%, Glycerin 0.2% and Hypromellose 0.3%. Preservative: POLYQUAD* (polyquaternium-1) 0.001%. Inactives: boric acid, calcium chloride, glycine, hydrochloric acid and/or sodium hydroxide (to adjust pH), magnesium chloride, polysorbate 80, potassium chloride, purified water, sodium chloride, zinc chloride.
TAMPER EVIDENT: For your protection, this bottle has an imprinted seal around the neck. Do not use if seal is damaged or missing at time or purchase.
Store at room temperature.
Alcon
Distributed by:
ALCON LABORATORIES, INC.
Fort Worth, Texas 76134 USA
LOT: EXP:
300048635-0621